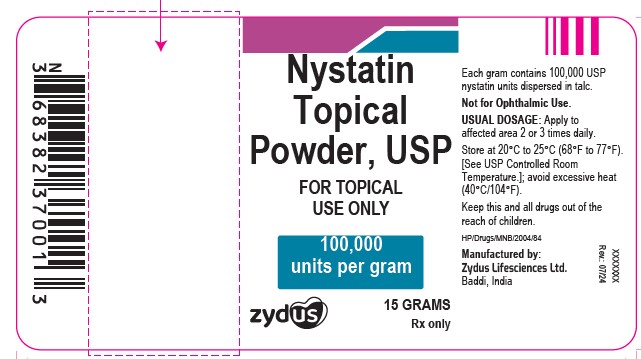 DRUG LABEL: NYSTATIN
NDC: 70771-1585 | Form: POWDER
Manufacturer: Zydus Lifesciences Limited
Category: prescription | Type: HUMAN PRESCRIPTION DRUG LABEL
Date: 20241203

ACTIVE INGREDIENTS: NYSTATIN 100000 [USP'U]/1 g
INACTIVE INGREDIENTS: TALC

Nystatin Topical Powder, USP

PACKAGE LABEL.PRINCIPAL DISPLAY PANEL

NDC 70771-1585-1

Nystatin Topical Powder, USP

FOR TOPICAL USE ONLY

100,000 units per gram

Rx Only

15 GRAMS